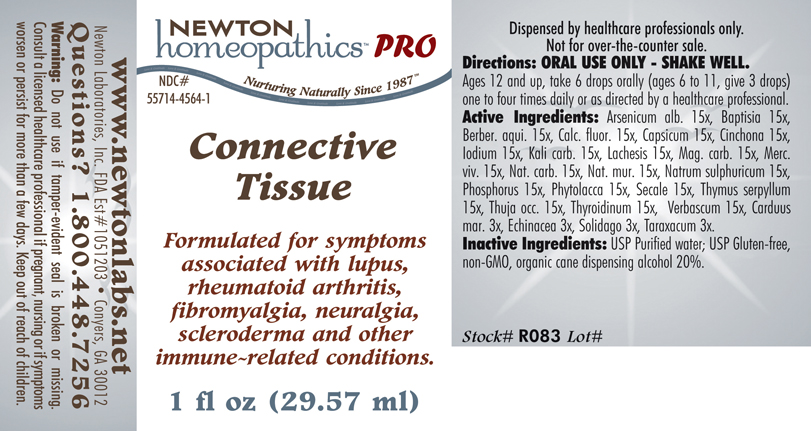 DRUG LABEL: Connective Tissue 
NDC: 55714-4564 | Form: LIQUID
Manufacturer: Newton Laboratories, Inc.
Category: homeopathic | Type: HUMAN PRESCRIPTION DRUG LABEL
Date: 20110601

ACTIVE INGREDIENTS: Arsenic Trioxide 15 [hp_X]/1 mL; Baptisia Tinctoria 15 [hp_X]/1 mL; Mahonia Aquifolium Root Bark 15 [hp_X]/1 mL; Calcium Fluoride 15 [hp_X]/1 mL; Capsicum 15 [hp_X]/1 mL; Iodine 15 [hp_X]/1 mL; Potassium Carbonate 15 [hp_X]/1 mL; Lachesis Muta Venom 15 [hp_X]/1 mL; Magnesium Carbonate 15 [hp_X]/1 mL; Mercury 15 [hp_X]/1 mL; Sodium Carbonate 15 [hp_X]/1 mL; Sodium Chloride 15 [hp_X]/1 mL; Sodium Sulfate 15 [hp_X]/1 mL; Phosphorus 15 [hp_X]/1 mL; Phytolacca Americana Root 15 [hp_X]/1 mL; Claviceps Purpurea Sclerotium 15 [hp_X]/1 mL; Thuja Occidentalis Leafy Twig 15 [hp_X]/1 mL; Thymus Serpyllum 15 [hp_X]/1 mL; Thyroid, Unspecified 15 [hp_X]/1 mL; Verbascum Thapsus 15 [hp_X]/1 mL; Silybum Marianum Seed 3 [hp_X]/1 mL; Echinacea, Unspecified 3 [hp_X]/1 mL; Solidago Virgaurea Flowering Top 3 [hp_X]/1 mL; Taraxacum Officinale 3 [hp_X]/1 mL; Cinchona Bark 15 [hp_X]/1 mL
INACTIVE INGREDIENTS: Alcohol

Connective Tissue

INDICATIONS & USAGE SECTION

Connective Tissue Formulated for symptoms associated with lupus, rheumatoid arthritis, fibromyalgia, neuralgia, scleroderma and other immune-related conditions.

DOSAGE & ADMINISTRATION SECTION

Directions: ORAL USE ONLY - SHAKE WELL. Ages 12 and up, take 6 drops orally (ages 6 to 11, give 3 drops) one to four times daily or as directed by a healthcare professional.

ACTIVE INGREDIENT SECTION

Arsenicum alb. 15x, Baptisia 15x, Berber. aqui. 15x, Calc. fluor. 15x, Capsicum 15x, Cinchona 15x, Iodium 15x, Kali carb. 15x, Lachesis 15x, Mag. carb. 15x, Merc. viv. 15x, Nat. carb. 15x, Nat. mur. 15x, Natrum sulphuricum 15x, Phosphorus 15x, Phytolacca 15x, Secale 15x, Thymus serpyllum15x, Thuja occ. 15x, Thyroidinum 15x, Verbascum 15x, Carduus mar. 3x, Echinacea 3x, Solidago 3x, Taraxacum 3x.

INACTIVE INGREDIENT SECTION

Inactive Ingredients: USP Purified Water; USP Gluten-free, non-GMO, organic cane dispensing alcohol 20%.

PURPOSE SECTION

Formulated for symptoms associated with lupus, rheumatoid arthritis, fibromyalgia, neuralgia, scleroderma and other immune-related conditions.

QUESTIONS? SECTION

www.newtonlabs.net Newton Laboratories, Inc. FDA Est # 1051203 - Conyers, GA 30012
Questions? 1.800.448.7256

WARNINGS SECTION

Warning: Do not use if tamper - evident seal is broken or missing. Consult a licensed healthcare professional if pregnant, nursing or if symptoms worsen or persist for more than a few days. Keep out of reach of children.

PREGNANCY OR BREAST FEEDING SECTION

Consult a licensed healthcare professional if pregnant, nursing or if symptoms worsen or persist for more than a few days.

KEEP OUT OF REACH OF CHILDREN SECTION

Keep out of reach of children.